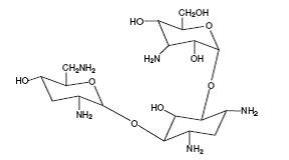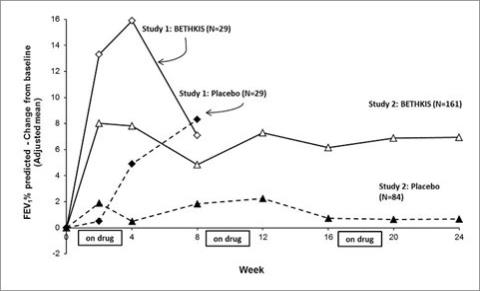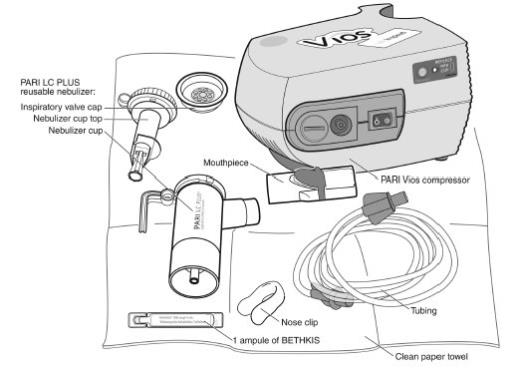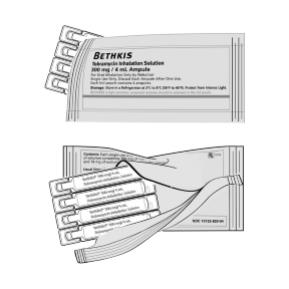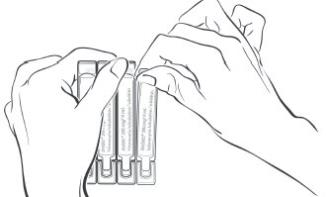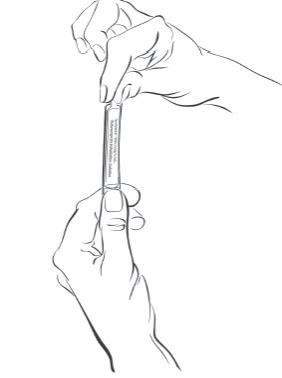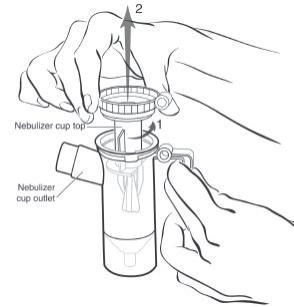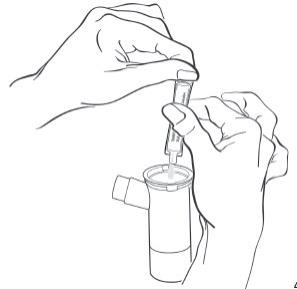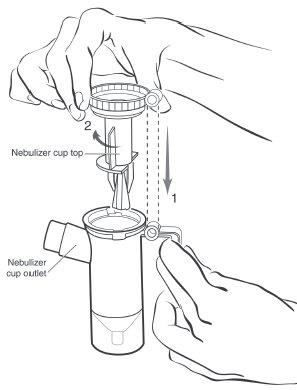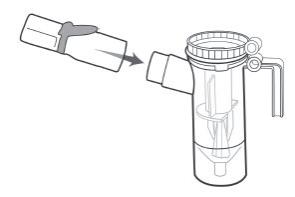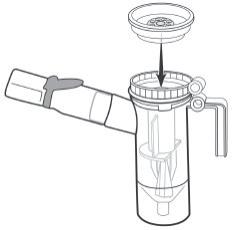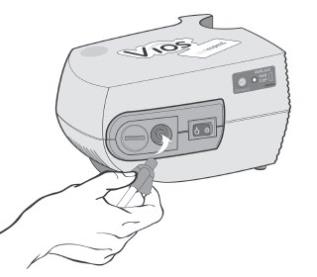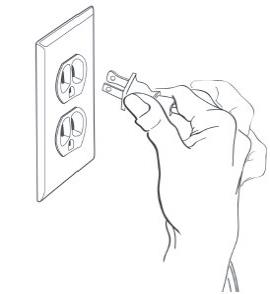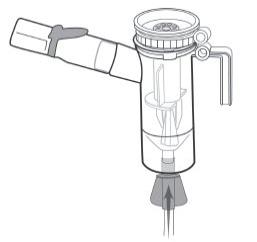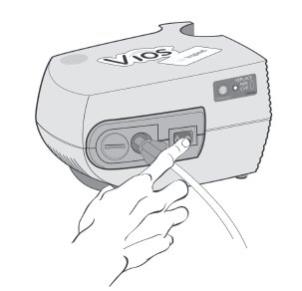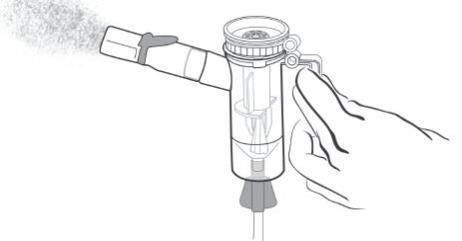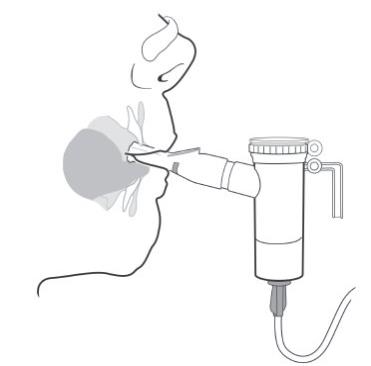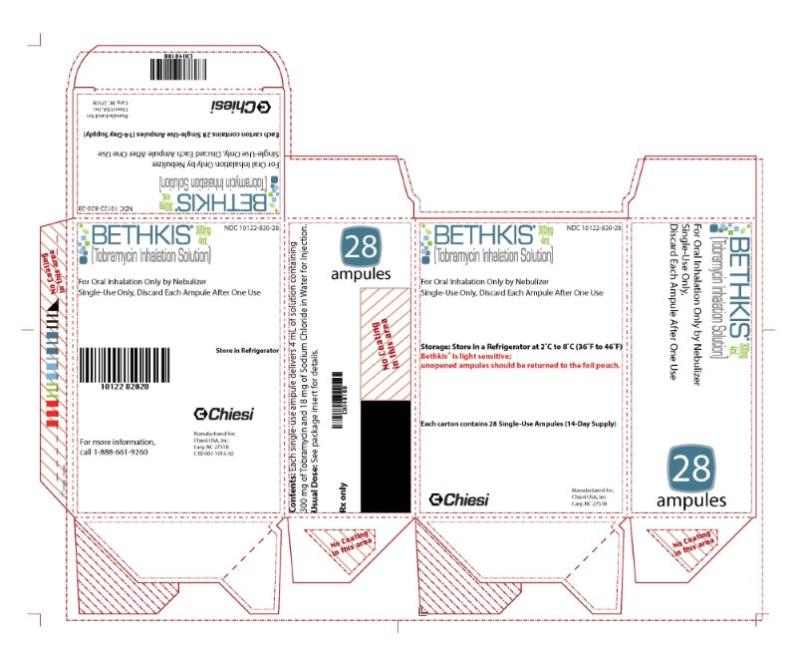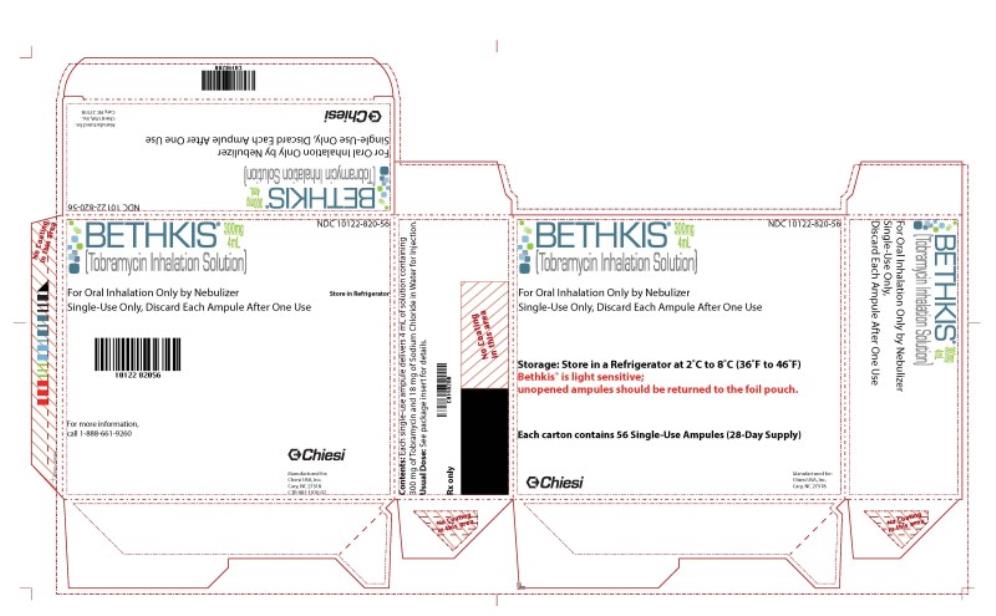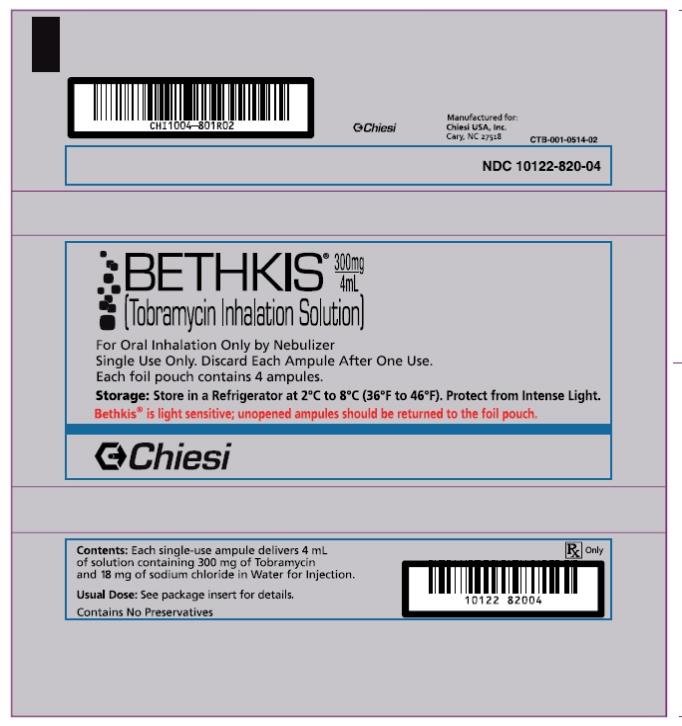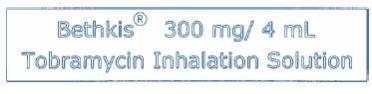 DRUG LABEL: BETHKIS
NDC: 10122-820 | Form: SOLUTION
Manufacturer: Chiesi USA, Inc.
Category: prescription | Type: HUMAN PRESCRIPTION DRUG LABEL
Date: 20230224

ACTIVE INGREDIENTS: TOBRAMYCIN 300 mg/4 mL
INACTIVE INGREDIENTS: SODIUM CHLORIDE; SULFURIC ACID; WATER; SODIUM HYDROXIDE

HIGHLIGHTS OF PRESCRIBING INFORMATION

These highlights do not include all the information needed to use BETHKIS safely and effectively. See full prescribing information for BETHKIS.
BETHKIS® (tobramycin inhalation solution), for oral inhalation use
Initial U.S. Approval: 1980

RECENT MAJOR CHANGES

Warnings and Precautions, Ototoxicity (5.1) | 2/2023

1 INDICATIONS AND USAGE

BETHKIS is an inhaled aminoglycoside antibacterial indicated for the management of cystic fibrosis patients with Pseudomonas aeruginosa. (1) Safety and efficacy have not been demonstrated in patients under the age of six years, patients with a forced expiratory volume in one second (FEV1) less than 40% or greater than 80% predicted, or patients colonized with Burkholderia cepacia. (1)

2 DOSAGE AND ADMINISTRATION

- For oral inhalation only (2.1)
- Administer the entire contents of one ampule twice daily by oral inhalation in repeated cycles of 28 days on drug, followed by 28 days off drug. (2.1)

3 DOSAGE FORMS AND STRENGTHS

Inhalation solution: 300 mg tobramycin per 4-mL solution in a single-use ampoule. (16)

4 CONTRAINDICATIONS

BETHKIS is contraindicated in patients with a known hypersensitivity to any aminoglycoside. (4)

5 WARNINGS AND PRECAUTIONS

- Caution should be exercised when prescribing BETHKIS to patients with known or suspected auditory, vestibular, renal, or neuromuscular dysfunction. (5.1, 5.2, 5.3 and 5.5)
- Aminoglycoside may aggravate muscle weakness because of a potential curare-like effect on neuromuscular function. (5.3)
- Bronchospasm can occur with inhalation of BETHKIS. (5.4)
- Audiograms, serum concentration, and renal function should be monitored as appropriate. (5.2 and 5.5)
- Fetal harm can occur when aminoglycosides are administered to a pregnant woman. Apprise women of the potential hazard to the fetus. (5.6)

6 ADVERSE REACTIONS

Common adverse reactions (more than 5%) occurring more frequently in BETHKIS patients are forced expiratory volume decreased, rales, red blood cell sedimentation rate increased, and dysphonia. (6.1)

To report SUSPECTED ADVERSE REACTIONS, contact Chiesi USA, Inc. at 1-888-661-9260 or FDA at 1-800-FDA-1088 or www.fda.gov/medwatch.

7 DRUG INTERACTIONS

- Concurrent and/or sequential use of BETHKIS with other drugs with neurotoxic, nephrotoxic or ototoxic potential should be avoided. (7.1)
- BETHKIS should not be administered concomitantly with ethacrynic acid, furosemide, urea, or intravenous mannitol. (7.2)

8 USE IN SPECIFIC POPULATIONS

- Aminoglycosides can cause fetal harm when administered to a pregnant woman. (8.1)
- Nursing mothers: discontinue drug or nursing, taking into consideration the importance of the drug to a mother. (8.2)

__________________________________________________________________

FULL PRESCRIBING INFORMATION

1 INDICATIONS AND USAGE

BETHKIS is indicated for the management of cystic fibrosis patients with Pseudomonas aeruginosa. Safety and efficacy have not been demonstrated in patients under the age of six years, patients with FEV1 less than 40% or greater than 80% predicted, or patients colonized with Burkholderia cepacia [see Clinical Studies (14)].

2 DOSAGE AND ADMINISTRATION

2.1 Dosage

Bethkis is for oral inhalation only [see Dosage and Administration (2.2)]. The recommended dosage of BETHKIS for patients six years of age and older is to administer one single-use ampule (300 mg/4 mL) twice daily by oral inhalation in repeated cycles of 28 days on drug, followed by 28 days off drug. The doses should be taken as close to 12 hours apart as possible and not less than 6 hours apart.

The 300 mg/4 mL dose of BETHKIS is the same for patients regardless of age or weight. BETHKIS has not been studied in patients less than six years old.

If patients miss a dose, they should take it as soon as possible anytime up to 6 hours prior to their next scheduled dose. If less than 6 hours remain before the next dose, wait until their next scheduled dose.

2.2 Administration Instructions

BETHKIS is administered by oral inhalation using a hand-held PARI LC PLUS Reusable Nebulizer with a PARI Vios Air compressor over an approximately 15 minute period and until sputtering from the output of the nebulizer has occurred for at least one minute. BETHKIS should not be diluted or mixed with dornase alfa or other medications in the nebulizer. BETHKIS is not for subcutaneous, intravenous, or intrathecal administration.

Further patient instructions on how to administer BETHKIS are provided in the Patient’s Instructions for Use [see Patient Counseling Information (17)].

BETHKIS should not be used if it is cloudy, if there are particles in the solution, or if it has been stored at room temperature for more than 28 days.

3 DOSAGE FORMS AND STRENGTHS

BETHKIS is supplied as a sterile, clear, colorless to pale yellow, non-pyrogenic, aqueous inhalational solution for nebulization in single-use 4 mL ampule containing 300 mg of tobramycin.

4 CONTRAINDICATIONS

BETHKIS is contraindicated in patients with a known hypersensitivity to any aminoglycoside.

5 WARNINGS AND PRECAUTIONS

5.1 Ototoxicity

Ototoxicity with use of BETHKIS

Caution should be exercised when prescribing BETHKIS to patients with known or suspected auditory or vestibular dysfunction.

Findings related to ototoxicity as measured by audiometric evaluations and auditory adverse event reports were similar between BETHKIS and placebo in controlled clinical trials. Hearing loss was reported in two (1.1%) BETHKIS-treated patients and in one (0.9%) placebo-treated patient during clinical studies. Additionally, dizziness and vertigo, both of which may be manifestations of vestibular forms of ototoxicity, were observed in similar numbers of BETHKIS- and placebo-treated patients. Dizziness occurred in two (1.1%) BETHKIS-treated patients and one (0.9%) placebo-treated patient and vertigo occurred in two (1.1%) BETHKIS-treated patients versus no placebo patients in clinical studies. None of the BETHKIS patients discontinued their therapy due to hearing loss, dizziness or vertigo.

Tinnitus may be a sentinel symptom of ototoxicity. No reports of tinnitus occurred in patients during clinical studies with BETHKIS, but because it has been observed with inhaled tobramycin solutions [see Adverse Reactions (6.2)], onset of this symptom warrants caution. Ototoxicity, manifested as both auditory and vestibular toxicity, has been reported with parenteral aminoglycosides. Vestibular toxicity may be manifested by vertigo, ataxia or dizziness. Patients with known or suspected auditory or vestibular dysfunction should be closely monitored when taking BETHKIS. Monitoring may include obtaining audiometric evaluations and serum tobramycin levels. If ototoxicity is noted, the patient should be managed as medically appropriate, including potentially discontinuing BETHKIS.

Risk of Ototoxicity Due to Mitochondrial DNA Variants

Cases of ototoxicity with aminoglycosides have been observed in patients with certain variants in the mitochondrially encoded 12S rRNA gene (MT-RNR1), particularly the m.1555A>G variant. Ototoxicity occurred in some patients even when their aminoglycoside serum levels were within the recommended range. Mitochondrial DNA variants are present in less than 1% of the general US population, and the proportion of the variant carriers who may develop ototoxicity as well as the severity of ototoxicity is unknown. In case of known maternal history of ototoxicity due to aminoglycoside use or a known mitochondrial DNA variant in the patient, consider alternative treatments other than aminoglycosides unless the increased risk of permanent hearing loss is outweighed by the severity of infection and lack of safe and effective alternative therapies.

5.2 Nephrotoxicity

Caution should be exercised when prescribing BETHKIS to patients with known or suspected renal dysfunction.

Nephrotoxicity was not seen during BETHKIS clinical studies but has been associated with aminoglycosides as a class. Patients with known or suspected renal dysfunction or taking concomitant nephrotoxic drugs along with BETHKIS should have serum concentrations of tobramycin and laboratory measurements of renal function obtained at the discretion of the treating physician. If nephrotoxicity develops, the patient should be managed as medically appropriate, including potentially discontinuing BETHKIS until serum concentrations fall below 2 mcg/mL.

Twenty-six (14%) BETHKIS patients and 15 (13%) placebo patients had increases in serum creatinine of at least 50% over baseline. Follow-up values were obtained for 17 of the 26 BETHKIS patients, all of which decreased to serum creatinine values that were within normal laboratory ranges. Patients who experience an increase in serum creatinine during treatment with BETHKIS should have their renal function closely monitored.

5.3 Neuromuscular Disorders

BETHKIS should be used cautiously in patients with muscular disorders.

Aminoglycosides, including tobramycin, may aggravate muscle weakness because of a potential curare-like effect on neuromuscular function. Neuromuscular blockade, respiratory failure, and prolonged respiratory paralysis may occur more commonly in patients with underlying neuromuscular disorders, such as myasthenia gravis or Parkinson’s disease. Prolonged respiratory paralysis may also occur in patients receiving concomitant neuromuscular blocking agents. If neuromuscular blockade occurs, it may be reversed by the administration of calcium salts but mechanical assistance may be necessary.

5.4 Bronchospasm

Bronchospasm has been reported with inhalation of tobramycin. In clinical studies with BETHKIS, bronchospasm was observed in one (0.5%) BETHKIS-treated patient and in no placebo-treated patients. Wheezing occurred in ten (5%) BETHKIS-treated patients and four (4%) placebo-treated patients. Bronchospasm and wheezing should be treated as medically appropriate.

5.5 Laboratory Tests

Audiograms

Clinical studies of inhaled tobramycin solutions did not identify hearing loss using audiometric tests which evaluated hearing up to 8000 Hz. Physicians should consider an audiogram for patients who show any evidence of auditory dysfunction, or who are at increased risk for auditory dysfunction. Tinnitus may be a sentinel symptom of ototoxicity, and therefore the onset of this symptom warrants caution.

Serum Concentrations

In patients with normal renal function treated with BETHKIS, serum tobramycin concentrations range from approximately 0.06-1.89 mcg/mL one hour after dose administration and do not require routine monitoring. Serum concentrations of tobramycin in patients with renal dysfunction or patients treated with concomitant parenteral tobramycin should be monitored at the discretion of the treating physician [see Clinical Pharmacology (12.3)].

The serum concentration of tobramycin should only be monitored through venipuncture and not finger prick blood sampling. Contamination of the skin of the fingers with tobramycin may lead to falsely increased measurements of serum levels of the drug. This contamination cannot be completely avoided by hand washing before testing.

Renal Function

The clinical studies of BETHKIS did not reveal any imbalance in the percentage of patients who experienced at least a 50% rise in serum creatinine from baseline in either the BETHKIS group (n=26, 14%) or the placebo group (n=15, 13%). Laboratory tests of urine and renal function should be conducted at the discretion of the treating physician.

5.6 Embryo-Fetal Toxicity

Aminoglycosides can cause fetal harm when administered to a pregnant woman. Aminoglycosides cross the placenta, and streptomycin has been associated with several reports of total, irreversible, bilateral congenital deafness in pediatric patients exposed in utero. However, systemic absorption of tobramycin following inhaled administration is expected to be minimal [see Clinical Pharmacology (12.3)]. Patients who use BETHKIS during pregnancy, or become pregnant while taking BETHKIS should be apprised of the potential hazard to the fetus [see Use in Specific Populations (8.1)].

5.7 Concomitant Use of Systemic Aminoglycosides

Patients receiving concomitant BETHKIS and parenteral aminoglycoside therapy should be monitored as clinically appropriate for toxicities associated with aminoglycosides as a class. Serum tobramycin levels should be monitored.

6 ADVERSE REACTIONS

6.1 Clinical Trials Experience

Because clinical trials are conducted under widely varying conditions, adverse reaction rates observed in clinical trials of drugs cannot be directly compared to rates in the clinical trials of another drug and may not reflect the rates observed in practice.

The data described below reflect exposure to BETHKIS in two placebo-controlled studies in 305 cystic fibrosis patients. Patients receiving BETHKIS ranged in age from 6 to 31 years.

In Study 1, an eight week study, 29 patients received BETHKIS versus 30 patients who received placebo for a total of four weeks on drug and four weeks off drug. All patients were ≤ 30 years of age (mean age 12.6 years) and 46% were females. 52.5% of patients were 6 to 12 years of age while 30.5% of patients were 13-17 years old. Only 16.5% of patients were adults (> 17 years old). Eighty percent (80%) of patients were chronically colonized with Pseudomonas aeruginosa while 20.3% of patients were initially or intermittently colonized with Pseudomonas aeruginosa during the study.

More patients in the placebo group discontinued/dropped out of Study 1 than in the BETHKIS group (23% [7/30] vs 3.4% [1/29], respectively). Five patients in the placebo group compared to none in the BETHKIS group discontinued/dropped out because of treatment-emergent adverse events (TEAEs) such as pulmonary exacerbations and respiratory disorders.

In Study 2, a 24 week study, 161 patients received BETHKIS versus 85 patients who received placebo in alternating four week on-off cycles for three cycles. All patients were ≤ 46 years of age (mean age 14.8 years) and 45% were females. 41% of patients were 6-12 years old while 29% of patients were 13-17 years old. Only 30% were adults (>17 years). Eighty-seven percent (87%) of patients were chronically colonized with P. aeruginosa. Only 13% were either initially or intermittently colonized with P. aeruginosa during the study.

More patients in the placebo group discontinued/dropped out of Study 2 than in the BETHKIS group (9.4% [8/85] vs 4.3% [7/161], respectively). Of these, 3 patients in the BETHKIS group (1.9%) compared to 2 patients in the placebo group (2.4%) withdrew due to a TEAE. The most common TEAEs causing patients to discontinue from the study drug are respiratory, thoracic, and mediastinal disorders.

The most common adverse experiences reported were respiratory disorders, consistent with the underlying disease in the patient population being evaluated and these were similarly distributed between both BETHKIS- and placebo-treated patients. The following adverse reactions were reported in at least 5% of Bethkis-treated patients and at rates ≥ 2% more common compared to the placebo-treated patients: decreased forced expiratory volume, rales, red blood cell sedimentation rate increased, and dysphonia (Table 1).

Table 1: Patients with Selected Treatment-Emergent Adverse Reactions Occurring in ≥ 2% of BETHKIS Patients
Adverse Reactions | BETHKIS N=190 (%) | Placebo N=115 (%)
Forced expiratory volume decreased | 59 (31%) | 33 (29%)
Rales | 36 (19%) | 18 (16%)
Red blood cell sedimentation rate increased | 16 (8%) | 6 (5%)
Dysphonia | 11 (6%) | 2 (2%)
Wheezing | 10 (5%) | 4 (4%)
Epistaxis | 6 (3%) | 0
Pharyngolaryngeal pain | 5 (3%) | 2 (2%)
Bronchitis | 5 (3%) | 1 (1%)
Tonsillitis | 4 (2%) | 0
Diarrhea | 3 (2%) | 1 (1%)
Eosinophilia | 3 (2%) | 0
Immunoglobulins increased | 3 (2%) | 0

6.2 Postmarketing Experience

The following adverse reactions have been identified during postapproval use of tobramycin inhalation solution. Because these reactions are reported voluntarily from a population of uncertain size, it is not always possible to reliably estimate their frequency or establish a causal relationship to drug exposure.

Ear and labyrinth disorders: Hearing loss, Tinnitus [see Warnings and Precautions (5.1)]

Skin and subcutaneous tissue disorders: Hypersensitivity, pruritus, urticaria, rash

Nervous system disorders: Aphonia, dysgeusia

Respiratory, thoracic, and mediastinal disorders:Bronchospasm [see Warnings and Precautions (5.4)], oropharyngeal pain

Metabolism and Nutrition Disorders: Decreased appetite

7 DRUG INTERACTIONS

7.1 Drugs with Neurotoxic, Nephrotoxic, or Ototoxic Potential

Concurrent and/or sequential use of BETHKIS with other drugs with neurotoxic, nephrotoxic, or ototoxic potential should be avoided.

7.2 Diuretics

Some diuretics can enhance aminoglycoside toxicity by altering antibiotic concentrations in serum and tissue. Therefore, BETHKIS should not be administered concomitantly with ethacrynic acid, furosemide, urea, or intravenous mannitol. The interaction between inhaled mannitol and BETHKIS has not been evaluated.

8 USE IN SPECIFIC POPULATIONS

8.1 Pregnancy

Risk Summary

Aminoglycosides can cause fetal harm. Published literature reports that use of streptomycin, an aminoglycoside, can cause total, irreversible, bilateral congenital deafness when administered to a pregnant woman [Warnings and Precautions (5.6)]. Although there are no available data on use of BETHKIS in pregnant women to be able to inform a drug-associated risk of major birth defects, miscarriage, or adverse maternal or fetal outcomes, systemic absorption of tobramycin following inhaled administration is expected to be minimal [see Clinical Pharmacology (12.3)]. There are risks to the mother associated with cystic fibrosis in pregnancy (see Clinical Considerations). In animal reproduction studies with subcutaneous administration of tobramycin in pregnant rats and rabbits during organogenesis there were no adverse developmental outcomes; however, ototoxicity was not evaluated in the offspring from these studies (see Data). Advise pregnant women of the potential risk to a fetus.

The estimated background risk of major birth defects and miscarriage for the indicated populations are unknown. All pregnancies have a background risk of birth defect, loss, or other adverse outcomes. In the U.S. general population, the estimated background risk of major birth defects and miscarriage in clinically recognized pregnancies is 2 to 4% and 15 to 20%, respectively.

Clinical Considerations

Disease-Associated Maternal and/or Embryo/Fetal Risk

Cystic fibrosis may increase the risk for preterm delivery.

Data

Animal Data

No reproduction toxicology studies have been conducted with inhaled tobramycin. However, subcutaneous administration of tobramycin at doses of up to 100 (rat) or 20 (rabbit) mg/kg/day during organogenesis was not associated with adverse developmental outcomes. Subcutaneous doses of tobramycin ≥ 40mg/kg/day were severely maternally toxic to rabbits and precluded the evaluation of adverse developmental outcomes. Ototoxicity was not evaluated in offspring during nonclinical reproductive toxicity studies with tobramycin.

8.2 Lactation

Risk Summary

There are no data on the presence of tobramycin in either human or animal milk, the effects on the breastfed infant, or the effects on milk production following oral inhalation of BETHKIS. Limited published data on other formulations of tobramycin in lactating women indicate that tobramycin is present in human milk. However, systemic absorption of tobramycin following inhaled administration is expected to be minimal [see Clinical Pharmacology (12.3)]. Tobramycin may cause alteration in the intestinal flora of the breastfeeding infant (see Clinical Considerations). The developmental and health benefits of breastfeeding should be considered along with the mother’s clinical need for BETHKIS and any potential adverse effects on the breastfed child from BETHKIS or from the underlying maternal condition.

Clinical Considerations

Tobramycin may cause intestinal flora alteration. Advise a woman to monitor the breastfed infant for loose or bloody stools and candidiasis (thrush, diaper rash).

8.4 Pediatric Use

The safety and efficacy of BETHKIS have not been studied in pediatric cystic fibrosis patients under six years of age.

8.5 Geriatric Use

Clinical studies of BETHKIS did not include patients aged 65 years and over. Tobramycin is known to be substantially excreted by the kidney, and the risk of adverse reactions to this drug may be greater in patients with impaired renal function. Because elderly patients are more likely to have decreased renal function, it may be useful to monitor renal function [see Warnings and Precautions (5.2, 5.5)].

8.6 Renal Impairment

Tobramycin is primarily excreted unchanged in the urine and renal function is expected to affect the exposure of tobramycin. The risk of adverse reactions to this drug may be greater in patients with impaired renal function. Patients with serum creatinine > 2mg/dL and blood urea nitrogen (BUN) > 40mg/dL have not been included in clinical studies and there are no data in this population to support a recommendation for or against dose adjustment [see Warnings and Precautions (5.2, 5.5)].

Serum concentrations of tobramycin in patients with renal dysfunction, or patients treated with concomitant parenteral tobramycin should be monitored at the discretion of the treating physician.

10 OVERDOSAGE

No overdoses have been reported with BETHKIS in clinical trials. Signs and symptoms of acute toxicity from overdosage of intravenous tobramycin might include dizziness, tinnitus, vertigo, loss of high-tone hearing acuity, respiratory failure, neuromuscular blockade, and renal impairment. Administration by inhalation results in low systemic bioavailability of tobramycin. Tobramycin is not significantly absorbed following oral administration. Tobramycin serum concentrations may be helpful in monitoring overdosage.

In all cases of suspected overdosage, physicians should contact the Regional Poison Control Center for information about effective treatment. In the case of any overdosage, the possibility of drug interactions with alterations in drug disposition should be considered.

11 DESCRIPTION

BETHKIS is a sterile, clear, colorless to pale yellow, non-pyrogenic, aqueous solution with pH and salinity adjusted. BETHKIS is administered by a compressed air driven reusable nebulizer. The chemical formula for tobramycin is C18H37N5O9 and the molecular weight is 467.52. Tobramycin is O-3-amino-3-deoxy-α-D-glucopyranosyl-(1→4)-O-[2,6-diamino- 2,3,6-trideoxy-α-D-ribo-hexopyranosyl-(1→6)]-2-deoxy-L‑streptamine.

The structural formula for tobramycin is:

Each single-use 4 mL ampule of BETHKIS contains one 300 mg dose of tobramycin, with sodium chloride and sulfuric acid in water for injection. Sulfuric acid and sodium hydroxide are used, as needed, to adjust the pH to 5.0. Nitrogen is used for sparging, filling and pouching. The formulation contains no preservatives.

12 CLINICAL PHARMACOLOGY

12.1 Mechanism of Action

BETHKIS is an aminoglycoside antibacterial [see Clinical Pharmacology (12.4)].

12.3 Pharmacokinetics

BETHKIS contains tobramycin, a cationic polar molecule that does not readily cross epithelial membranes.^1 The bioavailability of BETHKIS may vary because of individual differences in nebulizer performance and airway pathology.^2

Sputum Concentrations

Thirty minutes after inhalation of the first 300 mg dose of BETHKIS, the maximum geometric mean concentration of tobramycin was 814 mcg/g (ranging from 23 to 2843 mcg/g) in sputum. High variability of tobramycin concentration in sputum was observed. Three hours after inhalation started, sputum tobramycin concentrations declined to approximately 15% of those observed at 30 minutes. After four weeks of therapy with BETHKIS average mean sputum tobramycin concentrations obtained 10 minutes following administration were 717 mcg/g.

Distribution

Following administration of BETHKIS, tobramycin remains concentrated primarily in the airways. Binding of tobramycin to serum proteins is negligible.

Elimination

Tobramycin is not metabolized. The elimination half-life of tobramycin from serum is approximately two hours after intravenous (IV) administration. The elimination half-life following the inhalation of BETHKIS is approximately 4.4 hours. Assuming tobramycin absorbed following inhalation behaves similarly to tobramycin following intravenous administration, systemically absorbed tobramycin is eliminated principally by glomerular filtration. Unabsorbed tobramycin following inhalation is likely eliminated in expectorated sputum.

12.4 Microbiology

Mechanism of Action

Tobramycin, an aminoglycoside antibacterial, acts primarily by disrupting protein synthesis in the bacterial cell which eventually leads to death of the cell. Tobramycin has activity against a wide range of gram-negative bacteria including P. aeruginosa. It is bactericidal at or above the minimal inhibitory concentration (MIC) needed to inhibit growth of bacteria.

Mechanism of Resistance

The predominant mechanism of resistance to tobramycin in P. aeruginosa isolated from CF patients is impermeability and to a lesser extent enzymatic modification and other mechanisms which cumulatively lead to decreased susceptibility of P. aeruginosa to tobramycin.

Cross Resistance

Cross resistance between aminoglycosides exists but the cross resistance is variable.

Development of Resistance

Treatment for six months with BETHKIS in one clinical trial did not affect the susceptibility of the majority of P. aeruginosa isolates tested; however, increases in minimal inhibitory concentrations (MIC) were noted in some patients. The clinical significance of this information has not been clearly established in the treatment of cystic fibrosis patients.

Susceptibility Testing

The clinical microbiology laboratory should provide cumulative results of the in vitro susceptibility test results for antimicrobial drugs used in local hospitals and practice areas to the physicians as periodic reports that describe the susceptibility profile of nosocomial and community-acquired pathogens. These reports should aid the physician in selecting the most effective antimicrobial.

Susceptibility Testing Techniques

Dilution Techniques

Quantitative methods can be used to determine the minimum inhibitory concentration (MIC) of tobramycin that will inhibit the growth of the bacteria being tested. The MIC provides an estimate of the susceptibility of bacteria to tobramycin. The MIC should be determined using a standardized procedure.^(3, 5) Standardized procedures are based on a dilution method (broth or agar) or equivalent with standardized inoculum concentrations and standardized concentrations of tobramycin powder.

Diffusion Techniques

Quantitative methods that require measurement of zone diameters also provide reproducible estimates of the susceptibility of bacteria to antimicrobial compounds. One such standardized procedure requires the use of standardized inoculum concentrations.^(4, 5) This procedure uses paper disks impregnated with 10 mcg of tobramycin to test the susceptibility of bacteria to tobramycin.

Susceptibility Test Interpretive Criteria

In vitro susceptibility test interpretive criteria for inhaled tobramycin have not been determined. The relation of the in vitro MIC and/or disk diffusion susceptibility test results to clinical efficacy of inhaled tobramycin against the bacteria tested should be monitored.

Quality Control Parameters for Susceptibility Testing

In vitro susceptibility test quality control parameters exist for tobramycin so that laboratories that test the susceptibility of bacterial isolates to tobramycin can determine if the susceptibility test is performing correctly. Standardized dilution techniques and diffusion methods require the use of laboratory control bacteria to monitor the technical aspects of the laboratory procedures. Standard tobramycin powder should provide the following MIC and a 10 mcg tobramycin disk should produce the following zone diameters with the indicated quality control strains (Table 2).

Table 2: Acceptable Quality Control Ranges for Tobramycin
Bacteria | MIC Range (mcg/mL) | Disk Diffusion Zone Diameter (mm)
Pseudomonas æruginosa ATCC 27853 | 0.25-1 | 19-25

Other

No trends in the treatment-emergent isolation of other bacterial respiratory pathogens such as Burkholderia cepacia, Stenotrophomonas maltophilia, Achromobacter xylosoxidans, or Staphylococcus aureus were observed in clinical trials of BETHKIS relative to placebo. There was a slight increase in isolation of Candida spp in sputum at the end of the BETHKIS treatment cycle in clinical trials.

13 NONCLINICAL TOXICOLOGY

13.1 Carcinogenesis, Mutagenesis, Impairment of Fertility

A two-year rat inhalation toxicology study to assess carcinogenic potential of an inhaled solution of tobramycin has been completed. Rats were exposed to tobramycin for up to 1.5 hours per day for 95 weeks. Serum levels of tobramycin up to 35 mcg/mL were measured in rats, 35x the average 1 mcg/mL exposure levels observed in cystic fibrosis patients in clinical trials. There was no drug-related increase in the incidence of any variety of tumors.

Additionally, tobramycin has been evaluated for genotoxicity in a battery of in vitro and in vivo tests. The Ames bacterial reversion test, conducted with five tester strains, failed to show a significant increase in revertants with or without metabolic activation in all strains. Tobramycin was negative in the mouse lymphoma forward mutation assay, did not induce chromosomal aberrations in Chinese hamster ovary cells, and was negative in the mouse micronucleus test.

Subcutaneous administration of up to 100 mg/kg of tobramycin did not affect mating behavior or cause impairment of fertility in male or female rats.

14 CLINICAL STUDIES

Two, double-blind, randomized, placebo-controlled, parallel group clinical studies (Study 1 and Study 2), which randomized and dosed 306 patients, were conducted in cystic fibrosis patients with P. aeruginosa. The osmolality of the drug formulation used in these studies differed from the to-be-marketed product. To rely upon the efficacy and safety established in the placebo-controlled studies, an additional study was conducted as a bridge to the to-be-marketed drug. The bridging study assessed the efficacy and tolerability of aerosolized Tobramycin Inhalation Solution with osmolality similar to BETHKIS over a 4-week treatment in 324 patients with cystic fibrosis. Results of this study showed that the Tobramycin Inhalation Solution in this study had similar efficacy as that seen in the placebo-controlled studies.

The compressors in the placebo-controlled studies and the bridging study differed from the PARI VIOS compressor to be used with BETHKIS. In vitro cascade impaction studies demonstrated that the various compressors used in the clinical trials delivered equivalent doses and respirable fractions of the to-be-marketed BETHKIS and TOBI with the marketed compressor (PARI VIOS) when used with the same nebulizer (PARI LC Plus Reusable nebulizer).

All subjects enrolled in both efficacy studies had baseline FEV1 % predicted ≥ 40% and ≤ 80% (mean baseline FEV1 of 60% of predicted normal) and infected with P. aeruginosa. Subjects who were less than 6 years of age, or who had a baseline creatinine of ≥ 1.5 mg/dL, or who had Burkholderia cepacia isolated from sputum were excluded. A total of 190 patients, 29 in Study 1 and 161 in Study 2, received BETHKIS therapy on an outpatient basis. Of these, 55% were males and 45% were females. Eighty-two (43.2%) patients were between 6 and 12 years of age, 54 (28.4%) patients were between 13 and 17 years of age, and the remaining 54 (28.4%) patients were greater than 17 years of age. Of the patients who received BETHKIS, only 89.7% of patients in Study 1 had at least one concomitant medication, while all patients in Study 2 also received at least one concomitant medication. These concomitant medications include mucolytics, steroidal and nonsteroidal anti-inflammatory drugs, bronchodilators, rehabilitative physiotherapies and if necessary, antibiotics for bacterial infections other than P. aeruginosa.

Study 1

Study 1 was a double-blind, single cycle study that randomized 59 patients to receive BETHKIS (n=29) or placebo (n=30) for one cycle of treatment (28 days on treatment followed by 28 days off treatment). All patients were ≤ 30 years of age (mean age 12.6 years) and 46% were females. All randomized patients were included in the primary analysis except for one patient who had missing baseline information.

BETHKIS significantly improved lung function compared with placebo as measured by the absolute change in FEV1 % predicted from baseline to the end of Cycle 1 dosing in the primary analysis population. Treatment with BETHKIS and placebo resulted in absolute increases in FEV1 % predicted of 16% and 5%, respectively (LS mean difference = 11%; 95% CI: 3, 19; p=0.003). This analysis is adjusted for the covariate of baseline FEV1 % predicted, using multiple imputation for missing data. Figure 1 shows the average change in FEV1 % predicted over eight weeks.

Study 2

Study 2 was a randomized, double-blind, 3-cycle, placebo-controlled trial. A total of 247 eligible patients were randomized 2:1 to receive three cycles of BETHKIS (n=161) or placebo (n=86). As in Study 1, each cycle comprised 28 days on treatment followed by 28 days off treatment. All patients were ≤46 years of age (mean age 14.8 years) and 44.9% were females. In this study, two randomized patients in the placebo group were not included in the primary efficacy analysis; one withdrew consent without taking any trial medication and the other withdrew due to an adverse drug reaction.

BETHKIS significantly improved lung function compared with placebo as measured by the absolute change in FEV1 % predicted from baseline to the end of Cycle 3 “ON” period. Treatment with BETHKIS and placebo resulted in absolute increases in FEV1 % predicted of 7% and 1%, respectively (LS mean difference = 6%; 95% CI: 3, 10; p<0.001). This analysis is adjusted for the covariate of baseline FEV1 % predicted, using multiple imputation for missing data. Figure 1 shows the average change in FEV1 % predicted over 24 weeks from Study 2.

Figure 1: FEV 1 % of Predicted Normal – Absolute Change from Baseline (Adjusted mean) - ITT Population

In Study 2, 9.9% of patients treated with BETHKIS and 24.7% of patients who received placebo had unplanned hospitalizations due to the disease.

Also in Study 2, 6.2% of patients treated with BETHKIS and 16.5% of placebo patients received parenteral tobramycin.

15 REFERENCES

1. Neu HC. Tobramycin: an overview. [Review]. J Infect Dis. 1976; Suppl 134:S3-19.
2. Weber A, Smith A, Williams-Warren J, et al. Nebulizer delivery of tobramycin to the lower respiratory tract. Pediatr Pulmonol. 1994; 17(5):331-9.
3. Clinical and laboratory Standards Institute (CLSI) Methods for Dilution Antimicrobial Susceptibility Tests for Bacteria that Grow Aerobically: Approved Standard -9th edition. CLSI document M07-A9. CLSI 940 West Valley Rd. Suite 1400, Wayne PA 19087-1898. 2012
4. CLSI Performance Standards for Antimicrobial Susceptibility Testing: 22nd Informational supplement CLSI document M100-S22. CLSI 2012.
5. CLSI Performance standards for Antimicrobial Disk Susceptibility Tests: Approved standard -11th ed. CLSI document M02-A11. CLSI 2012.
6. PARI Vios Aerosol Delivery System with LC Plus Nebulizer: Instructions for Use. PARI Respiratory Equipment, Inc. 2010; 310D0028 Rev A 6-10.

16 HOW SUPPLIED/STORAGE AND HANDLING

16.1 How Supplied

BETHKIS 300 mg/4 mL is supplied as a sterile, clear, colorless to pale yellow, non-pyrogenic, aqueous solution and is available as follows:

- NDC 10122-820-56: 4 mL single-use ampule (carton of 14 foil pouches each containing four ampules)
- NDC 10122-820-28: 4 mL single-use ampule (carton of 7 foil pouches each containing four ampules)

16.2 Storage and Handling

BETHKIS should be stored under refrigeration at 2°C ‑ 8°C (36°F ‑ 46°F). Upon removal from the refrigerator, or if refrigeration is unavailable, BETHKIS pouches (opened or unopened) may be stored at room temperature [up to 25°C (77°F)] for up to 28 days. BETHKIS should not be used beyond the expiration date stamped on the ampule when stored under refrigeration 2°C ‑ 8°C (36°F ‑ 46°F) or beyond 28 days when stored at room temperature [up to 25°C (77°F)].

BETHKIS ampules should not be exposed to intense light. BETHKIS is light sensitive; unopened ampules should be returned to the foil pouch. The solution in the ampule is colorless to pale yellow, but may darken with age if not stored in the refrigerator; however, the color change does not indicate any change in the quality of the product as long as it is stored within the recommended storage conditions.

17 PATIENT COUNSELING INFORMATION

Advise the patient to read the FDA-approved patient labeling (Patient Information and Instructions for Use).

Information for Patients

Information on the long term efficacy and safety of BETHKIS is limited. There is no information in patients with severe cystic fibrosis (FEV1 < 40% predicted).

Patients should be advised to complete a full 28-day course of BETHKIS, even if they are feeling better. After 28 days of therapy, patients should stop BETHKIS therapy for the next 28 days, and then resume therapy for the next 28 day on and 28 day off cycle.

For patients taking several different inhaled medications and/or performing chest physiotherapy, advise the patient regarding the order they should take the therapies. It is recommended that BETHKIS be taken last.

BETHKIS is to be used with the PARI LC PLUS reusable nebulizer and the PARI VIOS air compressor. Refer to the manufacturer’s instructions for care and use of the nebulizer and compressor.

17.1 Ototoxicity

Inform patients that ototoxicity, as measured by complaints of hearing loss or tinnitus, was reported by patients treated with tobramycin. Physicians should consider an audiogram at baseline, particularly for patients at increased risk of auditory dysfunction.

If a patient reports tinnitus or hearing loss during BETHKIS therapy, the physician should refer that patient for audiological assessment.

Patients should be reminded that vestibular toxicity may manifest as vertigo, ataxia, or dizzines.

17.2 Bronchospasm

Inform patients that bronchospasm can occur with inhalation of tobramycin.

17.3 Risks Associated with Aminoglycosides

Inform patients of adverse reactions associated with aminoglycosides such as nephrotoxicity and neuromuscular disorders.

17.4 Laboratory Tests

Inform patients of the need to monitor hearing, serum concentrations of tobramycin, or renal function as necessary during treatment with BETHKIS.

17.5 Embryo-Fetal Toxicity

Inform patients that aminoglycosides can cause fetal harm when administered to a pregnant woman. Advise them to inform their doctor if they are pregnant, become pregnant, or plan to become pregnant.

17.6 Administration

Patients should be informed about what to do in the event they miss a dose of BETHKIS:

- In case a dose of BETHKIS is missed and there are at least 6 hours until the next dose, patients should be instructed to take the prescribed dose of BETHKIS as soon as possible. Otherwise, the missed dose should not be taken and the patient should resume the usual dosing schedule.
- Patients should be advised to contact their healthcare provider if they have questions.

17.7 Storage Instructions

You should store BETHKIS ampules in a refrigerator (36-46 °F or 2-8 °C). However, when you don’t have a refrigerator available (e.g., transporting your BETHKIS), you may store the foil pouches (opened or unopened) at room temperature (up to 77 °F/25 °C) for up to 28 days.

BETHKIS is light sensitive; unopened ampules should be returned to the foil pouch. Avoid exposing BETHKIS ampules to intense light. Unrefrigerated BETHKIS, which is normally colorless to pale yellow, may darken with age; however, the color change does not indicate any change in the quality of the product.

You should not use BETHKIS if it is cloudy, if there are particles in the solution, or if it has been stored at room temperature for more than 28 days. You should not use BETHKIS beyond the expiration date stamped on the ampule.

Nebulizers and Compressors: 1-800-327-8632

BETHKIS: 1-888-661-9260

U.S. Patent 6,987,094.

Manufactured for Chiesi USA, Inc.

by Woodstock Sterile Solutions, Inc.

Woodstock, Illinois 60098

© Chiesi USA, Inc. 2023

Printed in USA

CTB-004-1022-07-SPL

FDA-Approved Patient Labeling

Patient Information

BETHKIS®

(BETH kiss)

(tobramycin inhalation solution) for oral inhalation use

What is BETHKIS?

BETHKIS is a prescription medicine that is used to treat people with cystic fibrosis who have a bacterial infection called Pseudomonas aeruginosa. BETHKIS contains an antibacterial medicine called tobramycin (an aminoglycoside).

It is not known if BETHKIS is safe and effective:

- in children under 6 years of age
- in people who have decreased lung volume or a forced expiratory volume in one second (FEV1) less than 40% or greater than 80% predicted
- in people who are colonized with a bacterium called Burkholderia cepacian

Do not take BETHKIS if you are allergic to tobramycin, any of the ingredients in BETHKIS, or to any other aminoglycoside antibacterial.

See the end of this Patient Information for a complete list of ingredients in BETHKIS.

Before you take BETHKIS, tell your healthcare provider about all of your medical conditions, including if you:

- have or have had hearing problems (including noises in your ears such as ringing or hissing), hearing loss, or your mother has had hearing problems after taking an aminoglycoside.
- have been told you have certain gene variants (a change in the gene) related to hearing abnormalities inherited from your mother.
- have dizziness
- have or have had kidney problems
- have or have had problems with muscle weakness such as myasthenia gravis or Parkinson’s disease
- have or have had breathing problems such as wheezing, coughing, or chest tightness
- are pregnant or plan to become pregnant. BETHKIS is in a class of medicines that can harm your unborn baby and may be connected with complete deafness in babies at birth. The deafness affects both ears and cannot be changed.
- are breastfeeding or plan to breastfeed. It is not known if BETHKIS passes into your breast milk. Tobramycin, the medicine in BETHKIS may cause the following symptoms in your breastfed baby:
  - loose or bloody stools
  - yeast infection in the mouth or throat (thrush)
  - diaper rash

Call your baby’s healthcare provider if your breastfed baby has any of these problems. Talk to your healthcare provider about the best way to feed your baby during treatment with BETHKIS.

- are receiving aminoglycoside therapy by injection or through a vein (intravenous) while taking BETHKIS. Your blood levels of tobramycin will be checked.

Tell your healthcare provider about all the medicines you take, including prescription medicines, over-the-counter medicines, vitamins, and herbal supplements.

How should I take BETHKIS?

- See the step-by-step Instructions for Use at the end of this Patient Information leaflet about the right way to take your BETHKIS.
- Take BETHKIS exactly as your healthcare provider tells you to. Do not change your dose or stop taking BETHKIS unless your healthcare provider tells you to.
- The usual dose of BETHKIS for adults and children over 6 years of age is:
  - 1 single-use ampule of BETHKIS inhaled 2 times each day using your hand-held PARI LC PLUS Reusable Nebulizer with a PARI Vios air compressor.

- Each dose of BETHKIS should be taken as close to 12 hours apart as possible.
- You should not take your dose of BETHKIS less than 6 hours apart.
- BETHKIS is taken as a breathing treatment (inhalation) with a hand-held PARI LC Reusable Nebulizer with a PARI Vios air compressor. Do not use any other nebulizer for your BETHKIS treatment.
- Do not mix or dilute BETHKIS with dornase alfa or other medicines in your nebulizer system.
- Each treatment of BETHKIS should take about 15 minutes.
- BETHKIS should be inhaled while you are sitting or standing upright and breathing normally through the mouthpiece of the nebulizer. Nose clips may help you to breathe through your mouth.
- If you forget to take BETHKIS and there are at least 6 hours to your next dose, take your dose as soon as you can. Otherwise, wait for your next dose. Do not double the dose to make up for the missed dose.
- After taking BETHKIS for 28 days, you should stop taking it and wait 28 days. After you have stopped taking BETHKIS for 28 days, you should start taking BETHKIS again for 28 days. Complete the full 28-day course even if you are feeling better. It is important that you keep to the 28-day on, 28-day off cycle.

If you are taking several other medicines or treatments to treat your cystic fibrosis, you should take your medicines or other treatments before inhaling BETHKIS or as directed by your healthcare provider.

Taking BETHKIS with certain other medicines can cause serious side effects.

If you are taking BETHKIS, you should discuss with your healthcare provider if you should take:

- other medicines that may harm your nervous system, kidneys, or hearing
- “water pills” (diuretics) such as ethacrynic acid, furosemide, or intravenous mannitol
- Urea

Ask your healthcare provider or pharmacist for a list of these medicines, if you are not sure.

Know the medicines you take. Keep a list of them and show it to your healthcare provider and pharmacist when you get a new medicine.

- If you take too much BETHKIS, call your healthcare provider or go to the nearest hospital emergency room right away.

What are the possible side effects of BETHKIS?

BETHKIS can cause serious side effects, including:

- hearing loss or ringing in the ears (ototoxicity). Some people who were treated with tobramycin, the medicine in BETHKIS had hearing loss or ringing in the ears. Tell your healthcare provider right away if you have hearing loss or hear noises in your ears (such as ringing or hissing), or if you develop vertigo, dizziness, or difficulty with balance.
- worsening kidney problems (nephrotoxicity). Your healthcare provider may do a blood test and urine test to check how your kidneys are working while you are taking BETHKIS.
- worsening muscle weakness (neuromuscular disorder). BETHKIS can cause muscle weakness to get worse in people who already have problems with muscle weakness (myasthenia gravis or Parkinson’s disease).
- severe breathing problems (bronchospasm). Tell your healthcare provider right away if you get any of these symptoms of bronchospasm while taking BETHKIS:
  - shortness of breath with wheezing
  - coughing and chest tightness

The most common side effects of BETHKIS include:

- worsening of lung problems or cystic fibrosis
- noisy breathing (rales)
- abnormal red blood cell activity
- changes in your voice (hoarseness)

These are not all of the possible side effects of BETHKIS.

Call your doctor for medical advice about side effects. You may report side effects to FDA at 1-800-FDA-1088.

General information about the safe and effective use of BETHKIS.

Medicines are sometimes prescribed for purposes other than those listed in a Patient Information leaflet. Do not use BETHKIS for a condition for which it was not prescribed. Do not give BETHKIS to other people, even if they have the same symptoms that you have. It may harm them.

You can ask your pharmacist or healthcare provider for more information about BETHKIS that is written for health professionals.

What are the ingredients in BETHKIS?

Active ingredient: tobramycin

Inactive ingredients: sodium chloride, sulfuric acid in water for injection, and sodium hydroxide (for pH adjustment)

What is Psuedomonas aeriguinosa?

It is a very common bacterium that infects the lungs of nearly everyone with cystic fibrosis at some time during their lives. Some people do not get this infection until later in their lives, while others get it very young. It is one of the most damaging bacteria for people with cystic fibrosis. If the infection is not properly managed, it will continue to damage your lungs causing further problems to your breathing.

For more information, go to www.bethkis.com or call 1-888-661-9260.

This Patient Information has been approved by the U.S. Food and Drug Administration. 2/2023

Instructions for Use

BETHKIS®

(BETH kiss)

(tobramycin inhalation solution)

Follow the instructions below for taking BETHKIS. If you have any questions, ask your healthcare provider or pharmacist.

BETHKIS is available as a 28-day supply containing 56 ampules including 14 foil pouches and as a 14-day supply containing 28 ampules including 7 foil pouches. Each foil pouch contains 4 BETHKIS ampules.

Supplies you will need to take BETHKIS (See Figure A):

- 1 ampule of BETHKIS
- PARI LC PLUS reusable nebulizer
- PARI Vios compressor
- tubing to connect the nebulizer and compressor
- clean paper or cloth towels
- nose clips (optional)

(Figure A)

BETHKIS is used only in a PARI LC PLUS re-usable Nebulizer connected to a PARI LC PLUS Vios air compressor. Make sure you know how to use your nebulizer machine before you use it to breathe in BETHKIS.

Do not mix BETHKIS with other medicines in your nebulizer.

BETHKIS comes in a sealed foil pouch. Do not open a sealed pouch until you are ready to use a dose of BETHKIS. After opening the pouch, unused ready-to-use ampules should be returned to, and stored in, the pouch.

Getting ready:

- Put your PARI LC PLUS Reusable Nebulizer Top and Bottom (Nebulizer Cup) Assembly, Inspiratory Valve Cap, Mouthpiece with Valve, and Tubing on a clean and dry surface.
- Wash your hands with soap and water.

Preparing your BETHKIS dose:

Step 1: Open foil pouch. (See Figure B)

(Figure B)

Step 2: Separate 1 ampule by gently pulling apart at the bottom tabs (See Figure C) and use it right away.

(Figure C)

Step 3: Hold the bottom tab on the BETHKIS ampule with 1 hand (See Figure D). With your other hand, hold the top of the ampule and twist off the top of the ampule (See Figure D).

- Do not squeeze the ampule until you are ready to squeeze all the medicine into the Nebulizer Cup.

(Figure D)

Step 4: Hold the Nebulizer Cup and twist off the Nebulizer Cup Top in a counter-clockwise direction (See Figure E). Set the Top aside on a clean, dry surface.

(Figure E)

Step 5: Squeeze all of the medicine from the ampule into the Nebulizer Cup (See Figure F).

(Figure F)

Step 6: Line up the semi-circle on the Nebulizer Cup Top with the Nebulizer Cup Outlet and twist on the Nebulizer Cup Top in a clock-wise direction until it is tight. (See Figure G).

(Figure G)

Step 7: Push the mouthpiece straight onto the Nebulizer Cup Outlet (See Figure H).

(Figure H)

Step 8: Firmly push the Inspiratory Valve Cap straight down onto the Nebulizer Cup Top (See Figure I). The Inspiratory Valve Cap should fit tightly.

(Figure I)

Step 9: Connect 1 end of the tubing to the compressor air outlet. The tubing should fit tightly (See Figure J).

(Figure J)

Step 10: Plug your compressor plug into an electrical outlet (See Figure K).

(Figure K)

Step 11: Hold the Nebulizer Cup upright and firmly push the free end of the tubing straight up onto the Air Intake on the bottom of the Nebulizer Cup (See Figure L). Make sure to keep the Nebulizer Cup upright.

(Figure L)

Giving your BETHKIS dose:

Step 12: Turn on the compressor (Figure M) and check the Mouthpiece. You should see a steady mist coming from the Mouthpiece (Figure N).

- If you do not see a steady mist coming from the mouthpiece, check all tubing connections and make sure that the compressor is working the right way.

(Figure M)

(Figure N)

Step 13: Sit or stand in a comfortable, upright position that will let you breathe normally. Place the Mouthpiece between your teeth and on top of your tongue and breathe normally only through your mouth (See Figure O).

- Nose clips may help you breathe only through your mouth and not through your nose.

(Figure O)

Step 14: Keep breathing in your BETHKIS dose for at least 15 minutes. You will know that you have received your full dose of medicine when you hear a “spitting noise” coming from the Mouthpiece for at least 1 minute and the Nebulizer Cup is empty.

After your BETHKIS Dose:

Step 15: Clean and disinfect your nebulizer (see manufacturer’s instructions).

Care and Use of Your PARI Vios® Compressor

Follow the manufacturer’s instructions for care and use of your compressor.

How should I store BETHKIS?

- Store BETHKIS in the refrigerator at 36°F to 46°F (2°C to 8°C) until needed.
- After removing from the refrigerator, or if refrigeration is not available, BETHKIS foil pouches (opened or unopened) may be stored at room temperature up to 77 °F (25 °C) for up to 28 days.
- If BETHKIS is not stored in the refrigerator but at room temperature up to 77 °F (25 °C) it may turn dark. If BETHKIS turns dark, it does not change how well BETHKIS works. BETHKIS can still be used as long as it is stored at room temperature up to 77 °F (25 °C).
- Do not use BETHKIS after the expiration date printed on the ampule.
- Keep BETHKIS ampules in the foil pouch and away from light.
- Return unopened ampules to the foil pouch
- Keep BETHKIS and all medicines out of the reach of children.

This Patient Information and Instructions for Use have been approved by the U.S. Food and Drug Administration

Manufactured for Chiesi USA, Inc.

by Woodstock Sterile Solutions, Inc.

Woodstock, Illinois 60098

All trademarks referenced herein are the property of their prospective owners.

Issued: 2/2023

CTB-006-1022-06-SPL

PACKAGE/LABEL PRINCIPAL DISPLAY PANEL - 14 day

NDC 10122-820-28

Bethkis®

(Tobramycin Inhalation Solution)

300 mg/ 4 mL

For Oral Inhalation Only by Nebulizer

Single Use Only, Discard Each Ampule After One Use

Contents: Each single-use ampule delivers 4 mL of solution containing
300 mg of Tobramycin and 18 mg of Sodium Chloride in Water for Injection.
Usual Dose: See package insert for details.

Rx only

Storage: Store in a Refrigerator at 2°C to 8°C (36°F to 46°F).

Bethkis® is light sensitive;
unopened ampules should be returned to the foil pouch.

Each carton contains 28 Single-Use Ampules (14-Day Supply)

PACKAGE/LABEL PRINCIPAL DISPLAY PANEL - carton label

NDC 10122-820-56

Bethkis®

(Tobramycin Inhalation Solution)

300 mg/ 4 mL

For Oral Inhalation Only by Nebulizer

Single Use Only, Discard Each Ampule After One Use

Contents: Each single-use ampule delivers 4 mL of solution containing
300 mg of Tobramycin and 18 mg of Sodium Chloride in Water for Injection.
Usual Dose: See package insert for details.

Rx only

Storage: Store in a Refrigerator at 2°C to 8°C (36°F to 46°F).

Bethkis® is light sensitive;
unopened ampules should be returned to the foil pouch.

Each carton contains 56 Single-Use Ampules (28-Day Supply)

PACKAGE/LABEL PRINCIPAL DISPLAY PANEL - pouch label

Bethkis foil pouch

NDC 10122-820-04

Bethkis®

Tobramycin Inhalation Solution

300 mg/ 4 mL Ampule

For Oral Inhalation Only by Nebulizer

Single Use Only. Discard Each Ampule After One Use.

Each foil pouch contains 4 ampules.

Storage: Store in a Refrigerator at 2°C to 8°C (36°F to 46°F). Protect from Intense Light.

Bethkis® is light sensitive; unopened ampules should be returned to the foil pouch.

Contents: Each single-use ampule delivers 4 mL
of solution containing 300 mg of Tobramycin
and 18 mg of sodium chloride in Water for Injection.

Usual Dose: See package insert for details.

Contains No Preservatives

Rx Only

PACKAGE/LABEL PRINCIPAL DISPLAY PANEL - ampule label

Bethkis® 300 mg/ 4 mL

Tobramycin Inhalation Solution